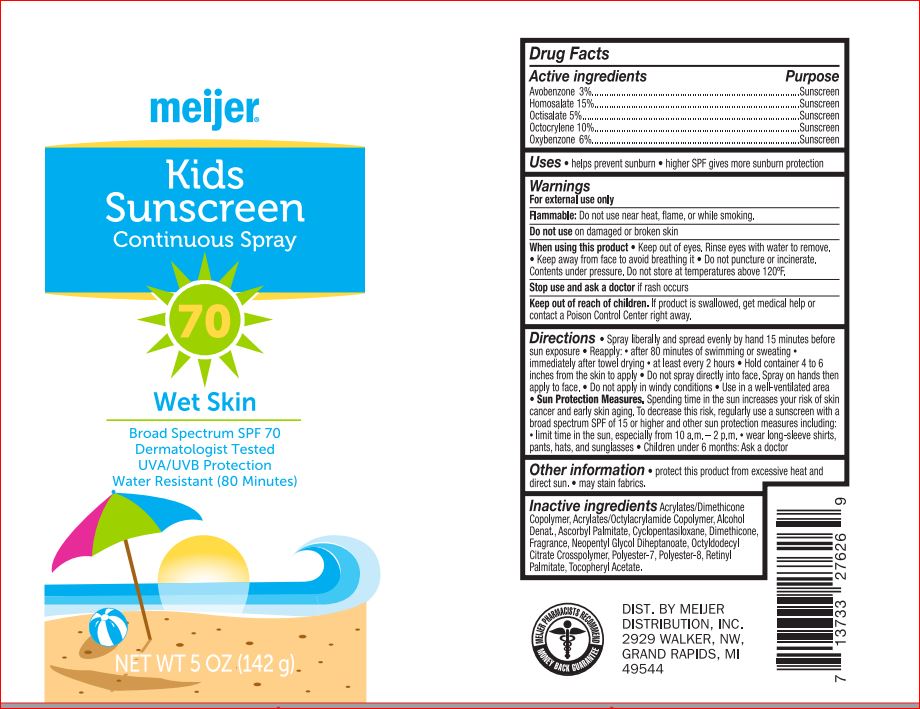 DRUG LABEL: Kids Sunscreen SPF 70
NDC: 41250-786 | Form: SPRAY
Manufacturer: Meijer
Category: otc | Type: HUMAN OTC DRUG LABEL
Date: 20180525

ACTIVE INGREDIENTS: Avobenzone 3 g/100 g; Homosalate 15 g/100 g; Octisalate 5 g/100 g; Octocrylene 10 g/100 g; Oxybenzone 6 g/100 g
INACTIVE INGREDIENTS: Alcohol; Ascorbyl Palmitate; CYCLOMETHICONE 5; Dimethicone; Neopentyl Glycol Diheptanoate; Polyester-7; POLYESTER-8 (1400 MW, CYANODIPHENYLPROPENOYL CAPPED); VITAMIN A PALMITATE; .ALPHA.-TOCOPHEROL ACETATE

Drug Facts

Active ingredients Purpose

Avobenzone 3.00%
Homosalate 15.00%
Octisalate 5.00%
Octocrylene 10.00%
Oxybenzone 6.00% Sunscreen

INDICATIONS AND USAGE

- helps prevent sunburn
-higher SPF gives more protection

Warnings

For external use only

Flammable: do not use near heat
Do not use on damaged or broken skin
When using this product keep out of eyes. Rinse with water to remove.
Stop use and ask a doctor if rash occurs
Keep out of reach of children. If product is swallowed, get medical help or contact a Poison Control Center right away.

Directions

spray liberally and spread evenly by hand 15 minutes before sun exposure
• reapply: • after 80 minutes of swimming or sweating
• immediately after towel drying • at least every 2 hours
• Sun Protection Measures. Spending time in the sun
increases your risk of skin cancer and early skin aging.
To decrease this risk, regularly use a sunscreen with a
broad spectrum SPF of 15 or higher and other sun
protection measures including:
• limit time in the sun, especially from 10 a.m. – 2 p.m.
• wear long-sleeve shirts, pants, hats, and sunglasses
• children under 6 months: Ask a doctor

Inactive ingredients

Acrylates/Dimethicone Copolymer
Acrylates/Octylacrylamide Copolymer
Alcohol Denat.
Ascorbyl Palmitate
Cyclopentasiloxane
Dimethicone
Fragrance
Neopentyl Glycol Diheptanoate
Octyldodecyl Citrate Crosspolymer
Polyester-7
Polyester-8
Retinyl Palmitate
Tocopheryl Acetate